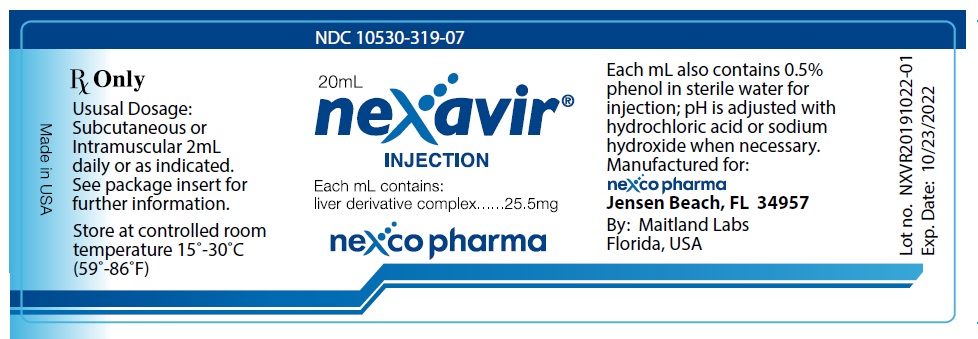 DRUG LABEL: NEXAVIR
NDC: 10530-319 | Form: INJECTION
Manufacturer: Nexco Pharma
Category: prescription | Type: HUMAN PRESCRIPTION DRUG LABEL
Date: 20200219

ACTIVE INGREDIENTS: PORK LIVER 25.5 mg/1 mL
INACTIVE INGREDIENTS: PHENOL; WATER; HYDROCHLORIC ACID; SODIUM HYDROXIDE

DESCRIPTION:

NEXAVIR® Injection (liver derivative complex) is a sterile solution containing 25.5mg liver derivative complex per ml in sterile water for injection.

NEXAVIR® Injection is composed of peptides and amino acids. The product contains no protein and does not exhibit anti-anemia activity.

NEXAVIR® Injection also contains as inactive ingredients: phenol 0.5%, sterile water for Injection, pH is adjusted with hydrochloric acid or sodium hydroxide when necessary.

CLINICAL PHARMACOI.OGY:

The specific action of NEXAVIR® is to enhance the resolution of inflammation and edema. In the late 1920's, it was demonstrated that liver was of benefit to patients suffering from acne vulgaris.^1 As a consequence, various techniques were employed for isolating the active "factor" from liver. Studies published in the late 1930's and early 1940's^2,3,4 showed activity in a specially purified liver fraction. During subsequent years, refinements in the isolation of the active material led to the marketing of NEXAVIR®.

Initially it was thought that the primary action of NEXAVIR® was on the capillaries and precapillary sphincters. However, it is now believed that this effect is a secondary one and that the primary action of NEXAVIR® is in response to injury at the cellular level. The capillary changes observed following administration of NEXAVIR® appear to be part of a more fundamental anti-inflammatory effect. In the normal animal, no consistent pharmacodynamic action has been demonstrated for NEXAVIR®. In particular, there is no effect on systemic blood pressure, no action on the autonomic nervous system and no alteration in prothrombin, coagulation or bleeding times. It is concluded that the specific action of the product is only apparent when tissues have been subjected to injury and when inflammation and edema are present.

INDICATIONS AND USAGE:

A wide range of dermatological clinical conditions benefit from NEXAVIR® therapy. The common denominator in these varied conditions is the presence of inflammation and edema. Favourable responses to the administration of NEXAVIR® in patients with acne vulgaris^5,6,7,8, herpes zoster, "poison ivy" dermatitis, pityriasis rosea, seborrheic dermatitis, urticaria and eczema^9,10,11, severe sunburn^12 and rosacea^13 have been reported.

CONTRAINDICATIONS:

Contraindicated in patients with hypersensitivity or intolerance to liver or pork products.

WARNING:

Use with caution in patients suspected of being hypersensitive to liver or with other allergic diatheses.

PRECAUTIONS:

Drug Interactions:
NEXAVIR® contains tyramine and should not be administered to patients taking MAO inhibitors because hypertensive crisis may occur.

Carcinogenesis, Mutagenesis, Impairment of Fertility:
No long-term animal studies have examined the carcinogenic or mutagenic potential of NEXAVIR®. NEXAVIR®s effect upon reproductive capacity is similarly unknown.

Pregnancy- Pregnancy Category C:
Animal reproduction studies have not been conducted with NEXAVIR®. It is also not known whether NEXAVIR® can cause fetal harm when administered to a pregnant woman or can affect reproduction capacity. NEXAVIR® should be given to a pregnant woman only if clearly needed.

Nursing Mothers:
It is not known whether this drug is excreted in human milk. Because many drugs are excreted in human milk, caution should be exercised when NEXAVIR® is administered to a nursing woman.

ADVERSE REACTIONS:

As with all Injectable medications, local reactions may occur. Local reactions may include pain. rash, stinging, swelling, and erythema.

DRUG ABUSE AND DEPENDENCE:

The Information on drug abuse and dependence is limited to uncontrolled data derived from marketing experience. Such experience has revealed no evidence of drug abuse and dependence associated with NEXAVIR® Injection.

DOSAGE AND ADMINISTRATION:

For the management of skin disorders, the usual dose of NEXAVIR® is 2 ml administered daily or as indicated. The product is given by intramuscular or subcutaneous injection only.

As with all parenteral drug products, NEXAVIR® should be inspected visually for particulate matter and discoloration prior to administration, whenever solution and container permit.

HOW SUPPLIED:

NEXAVIR® Injection (liver derivative complex, 25.5 mg/mL) is a sterile, brown solution
20 ml multiple dose vial NDC 10530-319-07

Store at controlled room temperature 15°-30°C (59°-86°F)

Manufactured for: Nexco Pharma, 10072 S. Ocean Drive, Suite 7N, Jensen Beach, Florida, 34957 (34957-2556)
Manufactured By: Maitland Labs, Florida, USA

Other information

Tel: +1-772-229-2992
Email: nexco@nexco-pharma.com

REFERENCES:

1. Sutton, R.L :. Liver Diets in Acne Vulgaris and in Furunculosis, Arch. Derm & Syph., 18:887, 1928. See also; Sutton, R.L, and Sutton, Jr, R.L.: Disease of the Skin, C.V. Mosby CO., St. Louis, 1939.
2. Marshall, V.: Further Studies on the Therapy of Acne Vulgaris with Modified Liver Extract. J . Invest. Derm.2:205, 1939.
3. Lichtenstein, M.A. and Stillians. A.W.: Liver Extract In Treatment of Acne Vulgaris in Tuberculosis Patients, Arch. Derm.& Syph.,45:959, 1942.
4. Boreen, C.A.: Boiled Liver In the Treatment of Acne Vulgaris, Minn. Med.,25:276, 1942.
5. Nierman, M.M.: Treatment of Cystic Acne Vulgaris with a Cutaneous Vasoconstrictor (Kutapressin) The Jour. of Ind. State Med. . Ass.n. 45:497,1952.
6. Knox. J.M.: Treatment of Cystic Acne with Kutapressin, U.S.N. News Letter, 20:9, 1952.
7. Lubowe, L.: Modern Treatment of Acne Vulgaris, Clin. Med. 59:8, 1952.
8. Pensky, N. and Goldber, N.: Treatment of Refractory Acne with Fractionated Type of Liver Extract, N.Y. State Jour. of Med. 53:2238, Oct. 1953
9. Burks, J.L, Jr.: The Modern Treatment of Acne Vulgaris, Jour. La. State Med. Soc. 106:92, 1954.
10. Burks,J. W and Knox, J.M.: S-Factor of Liver Extract In Acne Vulgaris, A.M.A. Archives of Derm. & Syphil., 70:508, 1954.
11. Barksdale, E. E.: The Use of S-Factor of Liver Extract (Kutapressin) in Dermatology, South. Med, Jour., 50:1524, 1957.
12. Heywood, H. W.: Use of Kutapressin in the treatment of Severe Sunburn, Clin. Med. 3:8, 1956.
13. Berrock, J.J.: Rosacea, Medical Times, 86:968, 1958

PACKAGE LABEL

NDC 10530-319-07

Nexavir Injection

20 mL multiple dose vial

Rx only